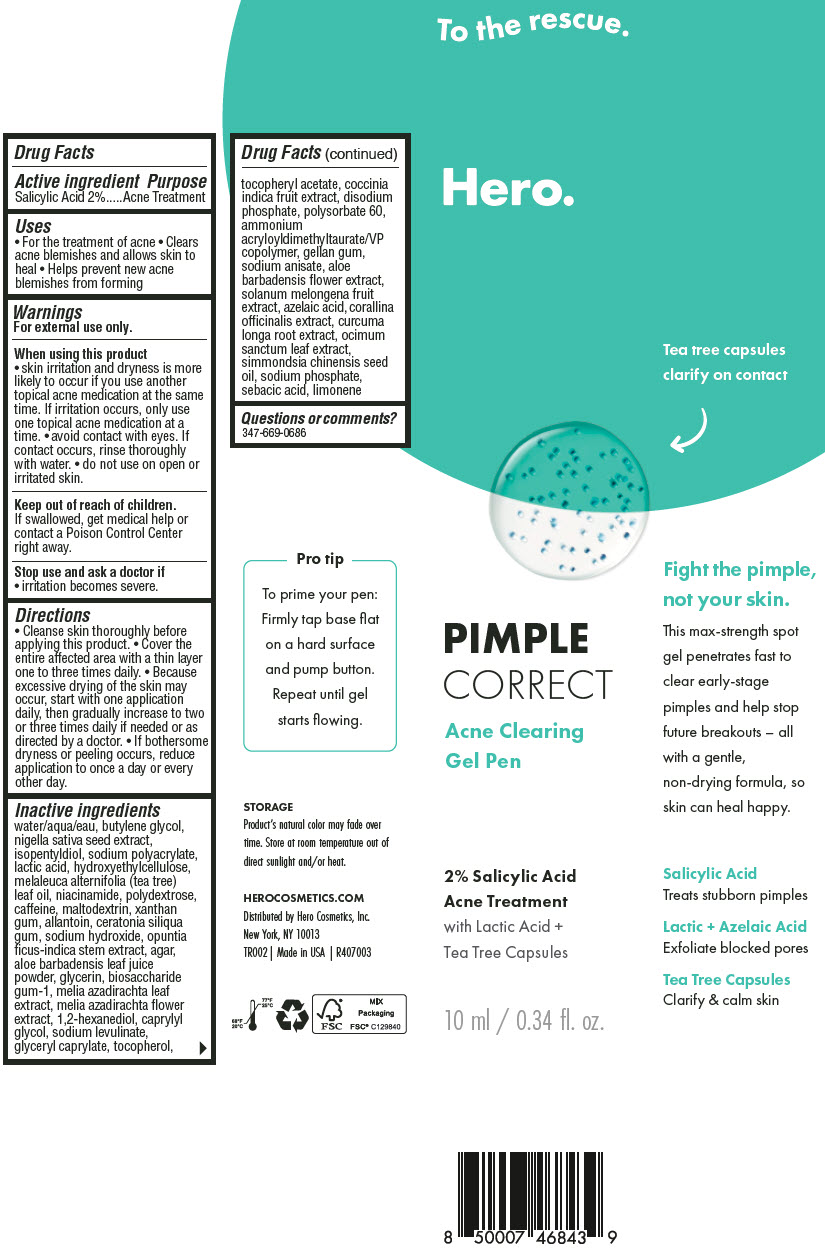 DRUG LABEL: Hero Cosmetics Pimple Correct Salicylic Acid Acne Treatment
NDC: 10237-003 | Form: GEL
Manufacturer: Church & Dwight Co., Inc.
Category: otc | Type: HUMAN OTC DRUG LABEL
Date: 20251205

ACTIVE INGREDIENTS: SALICYLIC ACID 20 mg/1 mL
INACTIVE INGREDIENTS: LIMONENE, (+)-; WATER; BUTYLENE GLYCOL; NIGELLA SATIVA SEED; ISOPENTYLDIOL; LACTIC ACID, UNSPECIFIED FORM; HYDROXYETHYL CELLULOSE, UNSPECIFIED; TEA TREE OIL; NIACINAMIDE; POLYDEXTROSE; CAFFEINE; MALTODEXTRIN; XANTHAN GUM; ALLANTOIN; LOCUST BEAN GUM; SODIUM HYDROXIDE; OPUNTIA FICUS-INDICA STEM; AGAR, UNSPECIFIED; ALOE VERA LEAF; GLYCERIN; BIOSACCHARIDE GUM-1; AZADIRACHTA INDICA LEAF; 1,2-HEXANEDIOL; CAPRYLYL GLYCOL; SODIUM LEVULINATE; GLYCERYL MONOCAPRYLATE; TOCOPHEROL; .ALPHA.-TOCOPHEROL ACETATE; COCCINIA GRANDIS FRUIT; SODIUM PHOSPHATE, DIBASIC, ANHYDROUS; POLYSORBATE 60; AMMONIUM ACRYLOYLDIMETHYLTAURATE/VP COPOLYMER; GELLAN GUM (LOW ACYL); SODIUM ANISATE; ALOE VERA FLOWER; AZELAIC ACID; CORALLINA OFFICINALIS; HOLY BASIL LEAF; JOJOBA OIL; SODIUM PHOSPHATE; SEBACIC ACID

Hero Cosmetics Pimple Correct Salicylic Acid Acne Treatment

Drug Facts

Active ingredient

Salicylic Acid 2%

Purpose

Acne Treatment

Uses

- For the treatment of acne
- Clears acne blemishes and allows skin to heal
- Helps prevent new acne blemishes from forming

Warnings

For external use only.

When using this product

- skin irritation and dryness is more likely to occur if you use another topical acne medication at the same time. If irritation occurs, only use one topical acne medication at a time.
- avoid contact with eyes. If contact occurs, rinse thoroughly with water.
- do not use on open or irritated skin.

Keep out of reach of children.

If swallowed, get medical help or contact a Poison Control Center right away.

Stop use and ask a doctor if

- irritation becomes severe.

Directions

- Cleanse skin thoroughly before applying this product.
- Cover the entire affected area with a thin layer one to three times daily.
- Because excessive drying of the skin may occur, start with one application daily, then gradually increase to two or three times daily if needed or as directed by a doctor.
- If bothersome dryness or peeling occurs, reduce application to once a day or every other day.

Inactive ingredients

water/aqua/eau, butylene glycol, nigella sativa seed extract, isopentyldiol, sodium polyacrylate, lactic acid, hydroxyethylcellulose, melaleuca alternifolia (tea tree) leaf oil, niacinamide, polydextrose, caffeine, maltodextrin, xanthan gum, allantoin, ceratonia siliqua gum, sodium hydroxide, opuntia ficus-indica stem extract, agar, aloe barbadensis leaf juice powder, glycerin, biosaccharide gum-1, melia azadirachta leaf extract, melia azadirachta flower extract, 1,2-hexanediol, caprylyl glycol, sodium levulinate, glyceryl caprylate, tocopherol, tocopheryl acetate, coccinia indica fruit extract, disodium phosphate, polysorbate 60, ammonium acryloyldimethyltaurate/VP copolymer, gellan gum, sodium anisate, aloe barbadensis flower extract, solanum melongena fruit extract, azelaic acid, corallina officinalis extract, curcuma longa root extract, ocimum sanctum leaf extract, simmondsia chinensis seed oil, sodium phosphate, sebacic acid, limonene

Questions or comments?

347-669-0686

Distributed by Hero Cosmetics, Inc.
New York, NY 10013

PRINCIPAL DISPLAY PANEL - 10 ml Tube Carton

Hero.

PIMPLE
CORRECT

Acne Clearing
Gel Pen

2% Salicylic Acid
Acne Treatment

with Lactic Acid +
Tea Tree Capsules

10 ml / 0.34 fl. oz.